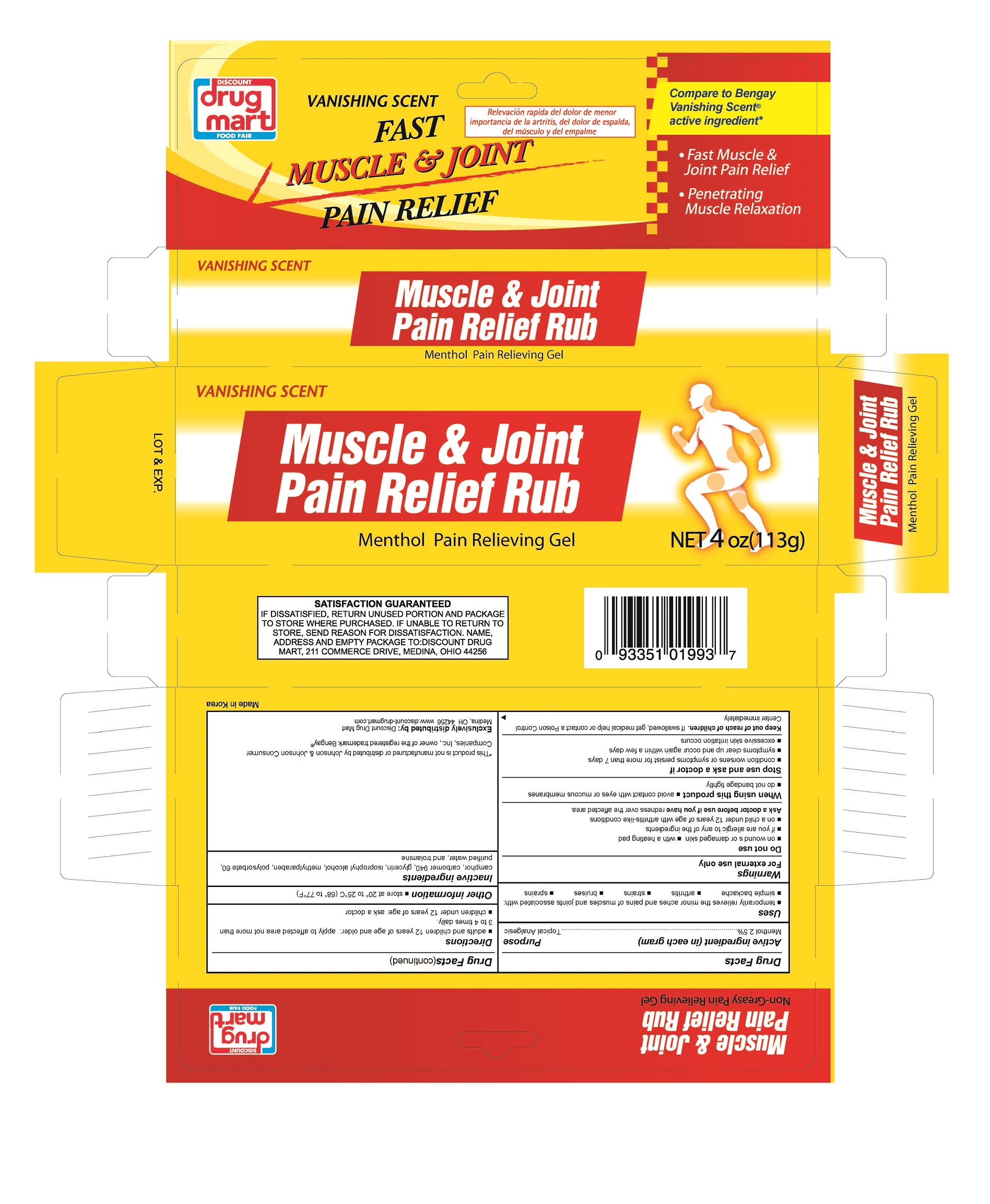 DRUG LABEL: Muscle and Joint
NDC: 53943-993 | Form: GEL
Manufacturer: Discount Drug Mart, Inc.
Category: otc | Type: HUMAN OTC DRUG LABEL
Date: 20151030

ACTIVE INGREDIENTS: MENTHOL 2.5 g/100 g
INACTIVE INGREDIENTS: CAMPHOR (SYNTHETIC); CARBOMER HOMOPOLYMER TYPE C; GLYCERIN; ISOPROPYL ALCOHOL; METHYLPARABEN; POLYSORBATE 60; WATER; TROLAMINE

Drug Facts

Active ingredient

Menthol 2.5%

Purpose

topical analgesic

Uses

For the temporary relief of minor aches and pains of muscles and joints associated with:

- simple backache
- arthritis
- strains
- bruises
- sprains

WARNINGS

For external use only

Do not use

- on wounds or damaged skin
- with a heating pad
- if you are allergic any of the ingredients
- on a child under 12 years of age with arthritis-like conditions

Ask a doctor before use if you have redness over the affected area

When using this product

- avoid contact with eyes or mucous membranes
- do not bandage tightly

Stop use and ask a doctor if

- condition worsens or symptoms persist for more than 7 days
- symptoms clear up and occur again within a few days
- excessive skin irritation occurs

Keep out of reach of children to avoid accidental ingestion.

If swallowed, get medical help or contact a Poison Control Center immediately.

Directions

- adults and children 12 years of age and older: apply to affected area not more than 3 to 4 times daily
- children under 12 years of age: ask a doctor

Other information

- store at 20° to 25°C (68° to 77°F)

Inactive ingredients

camphor, carbomer, glycerin, isoprophyl alcohol, methylparaben, polysorbate 60, purified water, trolamine

Package label

Muscle & Joint Pain Relief Gel